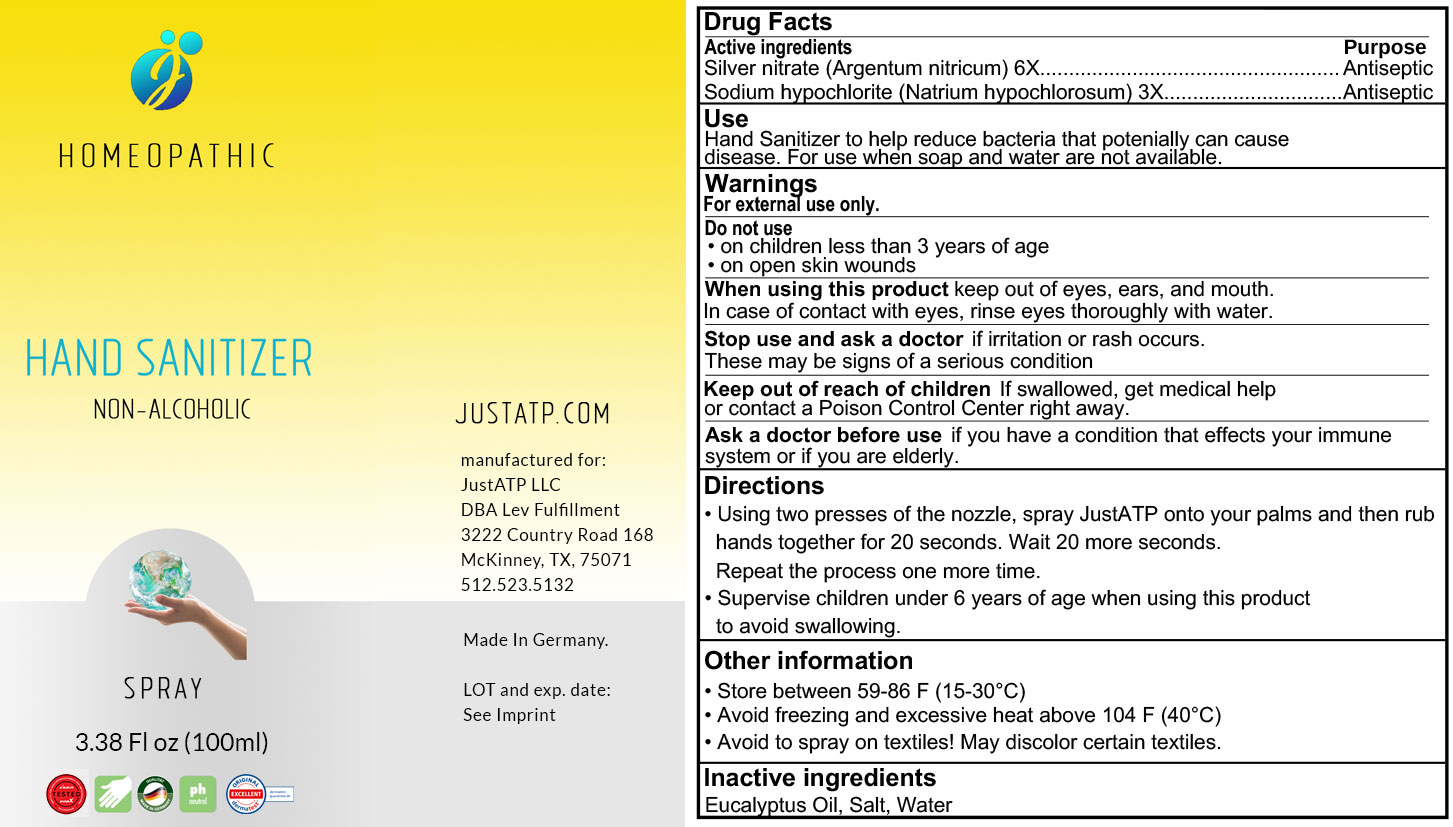 DRUG LABEL: JustATP - Non alcoholic - Homeopathic Hand Sanitizer
NDC: 81010-001 | Form: LIQUID
Manufacturer: JUSTATP LLC
Category: homeopathic | Type: HUMAN OTC DRUG LABEL
Date: 20220114

ACTIVE INGREDIENTS: SODIUM HYPOCHLORITE 3 [hp_X]/1000 mL; SILVER 6 [hp_X]/1000 mL
INACTIVE INGREDIENTS: SODIUM CHLORIDE; WATER; EUCALYPTUS OIL

JustATP - Non alcoholic - Homeopathic Hand Sanitizer

DOSAGE AND ADMINISTRATION

- Using two presess of the nozzle, spray JustATP onto your palms and then rub hands together for 20 seconds. Do the Smell Test* and wait 20 more seconds. Repeat the process one more time and do the Smell Test again.
- Supervise children under 6 years of age when using this product to avoid swallowing
- *Scan the QR code to see the Smell Test instructions on our site.

INACTIVE INGREDIENT

Water, Salty, Eucalyptus Oil.

INDICATIONS AND USAGE

Hand Sanitizer to help reduce bacteria that potentially can cause disease. For use when soap and water are not available.

ACTIVE INGREDIENT

Silver Nitrate (Argentum nitricum) 6X

Sodium hypochlorite (Natrium hypochlorosum) 3X

keep out of children

PURPOSE

Antiseptic

WARNINGS

- on children less than 2 months of age
- on open skin wounds

WHEN USING

keep out of eyes, ears, and mouth. In case of contact with eyes, rinse eyes thoroughly with water.

STOP USE

if irritation or rash occurs. These may be signs of a serious condition.

KEEP OUT OF REACH OF CHILDREN

If swallowed, get medical help or contact a Poison Control Center right away.

Ask a doctor before use have a condition that effects your immune system or if you are elderly.

OTHER SAFETY INFORMATION

- Store between 15-30C (59-86F)
- Avoid freezing and excessive heat above 40C (104 F)
- Do not apply to textiles! Check material compatibility. We accept no liability for improper use!